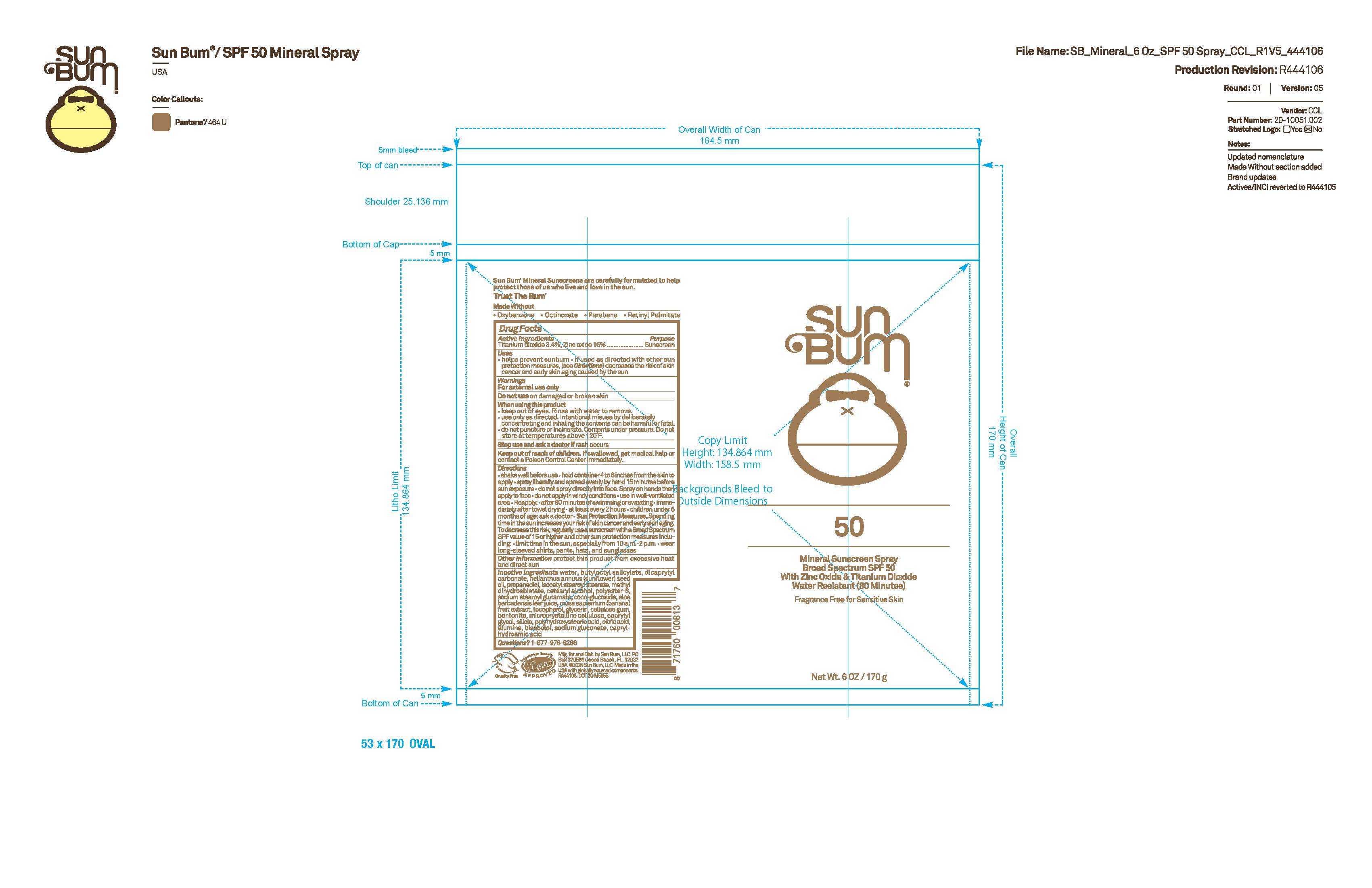 DRUG LABEL: Sun Bum 50 Mineral Sunscreen
NDC: 69039-733 | Form: SPRAY
Manufacturer: Sun Bum, LLC
Category: otc | Type: HUMAN OTC DRUG LABEL
Date: 20250814

ACTIVE INGREDIENTS: ZINC OXIDE 160 mg/1 g; TITANIUM DIOXIDE 34 mg/1 g
INACTIVE INGREDIENTS: POLYHYDROXYSTEARIC ACID (2300 MW); HELIANTHUS ANNUUS (SUNFLOWER) SEED OIL; SODIUM STEAROYL GLUTAMATE; MICROCRYSTALLINE CELLULOSE; ALUMINA; DICAPRYLYL CARBONATE; CELLULOSE GUM; PROPANEDIOL; ISOCETYL STEAROYL STEARATE; METHYL DIHYDROABIETATE; CAPRYLYL GLYCOL; GLYCERIN; COCO-GLUCOSIDE; SILICA DIMETHYL SILYLATE; BUTYLOCTYL SALICYLATE; CITRIC ACID; WATER; BISABOLOL; CAPRYLHYDROXAMIC ACID; POLYESTER-8 (1400 MW, CYANODIPHENYLPROPENOYL CAPPED); BANANA PEEL; SODIUM GLUCONATE; ALOE BARBADENSIS LEAF JUICE; TOCOPHEROL; BENTONITE; CETEARYL ALCOHOL

Sun Bum 50 Mineral Sunscreen

Active Ingredients

Titainium dioxide 3.4%, zinc oxide 16%

Purpose

Sunscreen

Uses

• helps prevent sunburn • if used as directed with other sun protection measures, (see Directions) decreases the risk of skin cancer and early skin aging caused by the sun

Warnings

For external use only

Flammable: do not use near hear, flame, or while smoking

Do not use on damaged or broken skin

When using this product

• keep out of eyes. Rinse with water to remove.

• use only as directed. Intentional misuse by deliberately concentrating and inhaling the contents can be harmful or fatal.

• do not puncture or incinerate. Contents under pressure. Do not store at temperatures above 120°F.

Stop use and ask a doctor if rash occurs

Keep out of reach of children. If swallowed, get medical help or contact a Poison Control Center immediately.

Warnings

Keep Out Of Reach Of Children

Directions

• shake well before use

• hold container 4 to 6 inches from the skin to apply

• spray liberally and spread evenly by hand 15 minutes before sun exposure

• do not spray directly onto face. Spray on hands then apply to face.

• do not apply in windy conditions

• use in a well-ventilated area

•Avoid inhaling or exposing others to spray

• reapply: after 80 minutes of swimming or sweating

• immediately after towel drying

• at least every 2 hours

• children under 6 months of age: ask a doctor

• Sun Protection Measures. Spending time in the sun increases your risk of skin cancer and early skin aging. To decrease this risk, regularly use a sunscreen with a Broad Spectrum SPF value of 15 or higher and other sun protection measures including:

• limit time in the sun, especially from 10 a.m.- 2 p.m.

• wear long-sleeved shirts, pants, hats and sunglasses

Directions

• shake well before use

• hold container 4 to 6 inches from the skin to apply

• spray liberally and spread evenly by hand 15 minutes before sun exposure

• do not spray directly onto face. Spray on hands then apply to face.

• do not apply in windy conditions

• use in a well-ventilated area

•Avoid inhaling or exposing others to spray

Other Information

protect this product from excessive heat and direct sun

Inactive Ingredients

water, butyloctyl salicylate, dicaprylyl carbonate, helianthus annuus (sunflower) seed oil, propanediol, iscocetyl stearoyl stearate, methyl dihydroabieate, cetearyl alcohol, polyester-8, sodium stearoyl glutamate, coco-glucoside, aloe barbadensis leaf juice, musa sapientum (banana) fruit extract, tocopherol, glycerin, cellulose gum, bentonite, microcrystalline cellulose, caprylyl glycol, silica, polyhydroxystearic acid, citric acid, alumina, bisabolol, sodium gluconate, caprylhydroamic acid

Questions?

1-877-978-6286